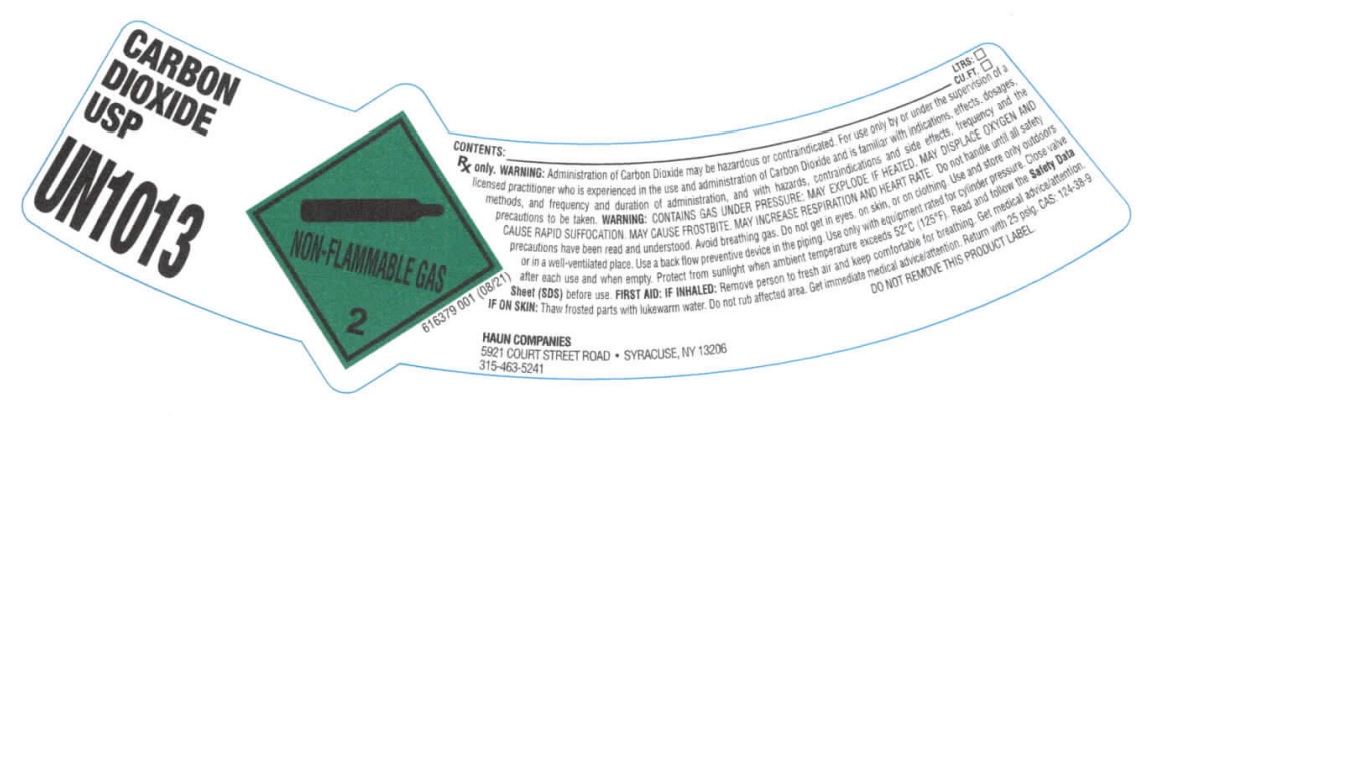 DRUG LABEL: Carbon Dioxide
NDC: 14961-009 | Form: GAS
Manufacturer: Haun Specialty Gases, Inc.
Category: prescription | Type: HUMAN PRESCRIPTION DRUG LABEL
Date: 20251229

ACTIVE INGREDIENTS: CARBON DIOXIDE 990 mL/1 L

Carbon Dioxide

PACKAGE LABEL

CARBON DIOXIDE USP

UN1013

CONTENTS: LTRS:

CU.FT:

Rx only. WARNING: Administration of Carbon Dioxide may be hazardous or contraindicated. For use only by or under the supervision of a licensed practitioner who is experienced in the use and administration of Carbon Dioxide and is familiar with indications, effects, dosages, methods, and frequency and duration of administration, and with hazards, contraindications and side effects, frequency and the precautions to be taken. WARNING: CONTAINS GAS UNDER PRESSURE; MAY EXPLODE IF HEATED. MAY DISPLACE OXYGEN AND CAUSE RAPID SUFFOCATION. MAY CAUSE FROSTBITE. MAY INCREASE RESPIRATION AND HEART RATE. Do not handle until all safety precautions have been read and understood. Avoid breathing gas. Do not get in eyes, on skin, or on clothing. Use and store only outdoors or in a well-ventilated place. Use a back flow preventive device in the piping. Use only with equipment rated for cylinder pressure. Close valve after each use and when empty. Protect from sunlight when ambient temperature exceeds 52 C (125 F). Read and follow the Safety Data Sheet (SDS) before use. FIRST AID: IF INHALED: Remove person to fresh air and keep comfortable for breathing. Get medical advice/attention. IF ON SKIN: Thaw frosted parts with lukewarm water. Do not rub affected area. Get immediate medical advice/attention. Return with 25 psig. CAS: 124-38-9

DO NOT REMOVE THIS PRODUCT LABEL

HAUN COMPANIES

5921 COURT STREET ROAD SYRACUSE, NY 13206

315-463-5241